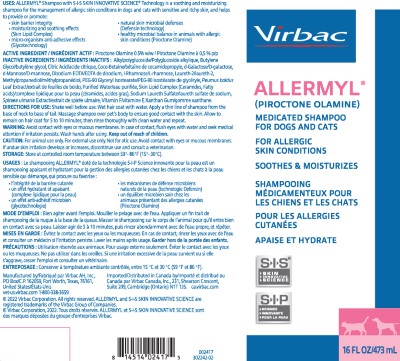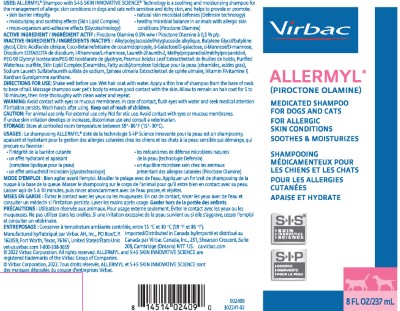 DRUG LABEL: Allermyl
NDC: 51311-071 | Form: SHAMPOO
Manufacturer: Virbac AH, Inc.
Category: animal | Type: OTC ANIMAL DRUG LABEL
Date: 20240222

ACTIVE INGREDIENTS: PIROCTONE OLAMINE 5 mg/1 mL

Allermyl® Medicated Shampoo

MEDICATED SHAMPOO FOR DOGS AND CATS FOR ALLERGIC SKIN CONDITIONS SOOTHES & MOISTURIZES S-I-S® ● SKIN ● INNOVATIVE ● SCIENCE

USES:

ALLERMYL® Shampoo with S-I-S SKIN INNOVATIVE SCIENCE® Technology is a soothing and moisturizing shampoo for the management of allergic skin conditions in dogs and cats with sensitive and itchy skin, and helps to provide or promote:

● skin barrier integrity

● moisturizing and soothing effects (Skin Lipid Complex)

● micro-organism anti-adhesive effects (Glycotechnology)

● natural skin microbial defenses (Defensin technology)

● healthy microbial balance in animals with allergic skin conditions (Piroctone Olamine)

ACTIVE INGREDIENTS:

Piroctone Olamine 0.5% w/w

INACTIVE INGREDIENTS:

Alkylpolyglucoside, Butylene Glycol, Citric Acid, Coco-Betaine, d-Galactose, d-Mannose, Disodium EDTA, l-Rhamnose, Laureth-2, Methylpropanediol, PEG-90 Glyceryl Isostearate, Peumus boldus Leaf Extract, Purified Water, Skin Lipid Complex (Ceramides, Fatty acids), Sodium Laureth Sulfate, Spiraea ulmaria Extract, Vitamin F, Xanthan Gum.

DIRECTIONS FOR USE:

Shake well before use. Wet hair coat with water. Apply a thin line of shampoo from the base of neck to base of tail. Massage shampoo over pet’s body to ensure good contact with the skin. Allow to remain on hair coat for 5 to 10 minutes, then rinse thoroughly with clean water and repeat.

WARNING:

Avoid contact with eyes or mucous membranes. In case of contact, flush eyes with water and seek medical attention if irritation persists. Wash hands after using. Keep out of reach of children.

CAUTION:

For animal use only. For external use only. Not for otic use. Avoid contact with eyes or mucous membranes. If undue skin irritation develops or increases, discontinue use and consult a veterinarian.

STORAGE:

Store at controlled room temperature between 59°-86°F (15°-30°C)

Manufactured by

Virbac AH, Inc.,

PO Box 162059,

Fort Worth, Texas,

76161, United States

vet-us.virbac.com

1-800-338-3659

© 2022 Virbac Corporation. All rights reserved. ALLERMYL and S-I-S SKIN INNOVATIVE SCIENCE are registered trademarks of the Virbac Group of Companies.

Imported/Distributed in Canada by

Virbac Canada, Inc.,

231 Shearson Crescent, Suite 209,

Cambridge (Ontario) N1T 1J5

ca.virbac.com